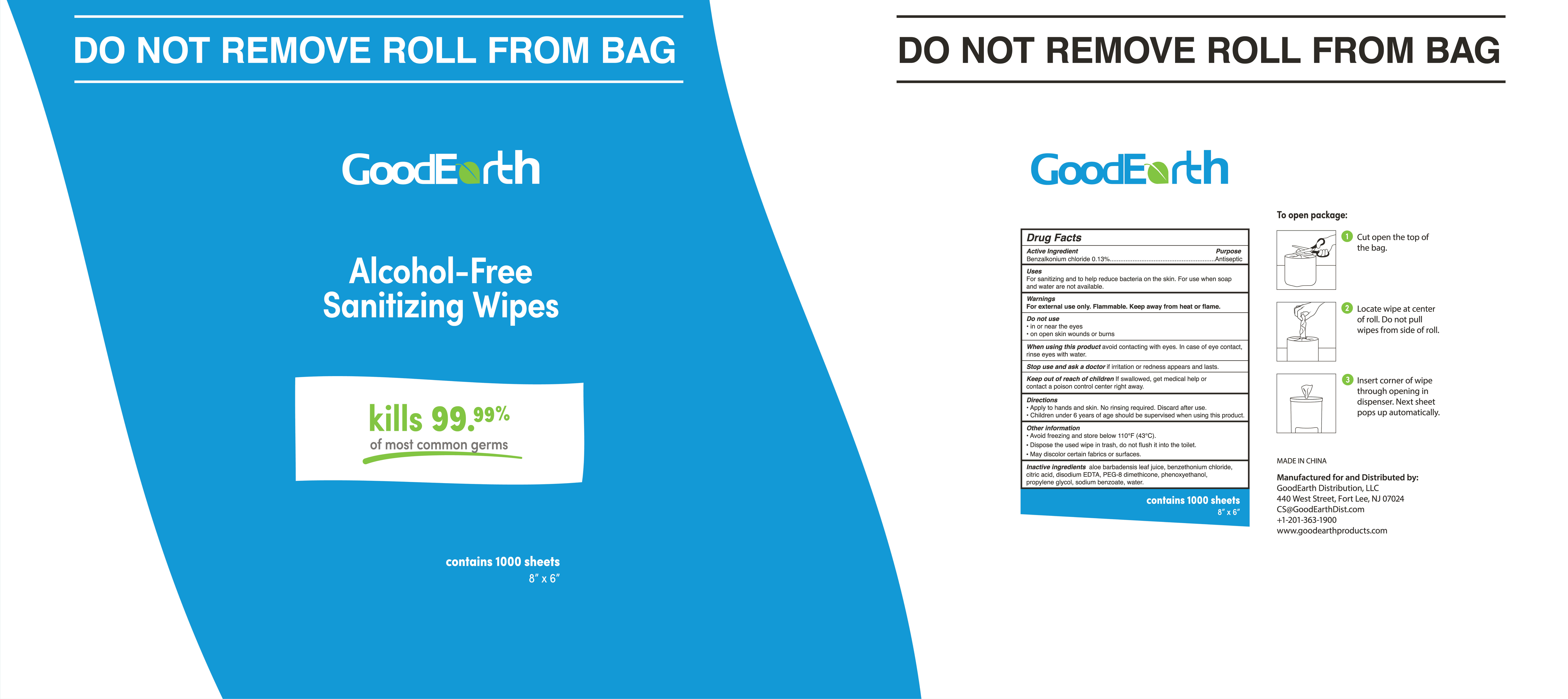 DRUG LABEL: Sanitizing Wipes
NDC: 78028-331 | Form: SWAB
Manufacturer: Dalian Da Xin Nonwoven Technology Co.,Ltd	
Category: otc | Type: HUMAN OTC DRUG LABEL
Date: 20221213

ACTIVE INGREDIENTS: BENZALKONIUM CHLORIDE 0.13 mg/100 mL
INACTIVE INGREDIENTS: CITRIC ACID MONOHYDRATE; SODIUM BENZOATE; ALOE VERA LEAF; WATER; PHENOXYETHANOL; PROPYLENE GLYCOL; PEG-8 DIMETHICONE; EDETATE DISODIUM ANHYDROUS; BENZETHONIUM CHLORIDE

Dalian Daxin-GoodEarth- BZK wipes 1000 PCS NEW code 2023

Active Ingredient(s)

Benzalkonium chloride 0.3%

Purpose

Antiseptic

Use

Hand Sanitizer to help reduce bacteria that potentially can cause disease. For use when soap and water are not available.

Warnings

For external use only. Flammable. Keep away from heat or flame

Do not use

in or near the eyes.
on open skin wounds or burns

When using this product keep out of eyes, ears, and mouth. In case of contact with eyes, rinse eyes thoroughly with water.
Stop use and ask a doctor if irritation or rash occurs. These may be signs of a serious condition.
Keep out of reach of children. If swallowed, get medical help or contact a Poison Control Center right away.

Stop use and ask a doctor if irritation or rash occurs. These may be signs of a serious condition.

Keep out of reach of children. If swallowed, get medical help or contact a Poison Control Center right away.

Directions

- Apply to hands and skin. No rinsing required. Discard after use.
- Children under 6 years of age should be supervised when using this product.

Other information

- Avoid freezing and store below 110F (43 C degrees).
- Dispose of the used wipe in the trash, do not flush it into the toilet.
- It may discolor certain fabrics or surfaces.

Inactive ingredients

propylene glycol, sodium benzoate, PEG-8 dimethicone, disodium edta, citric acid, phenoxyethanol, benzethonium chloride, aloe babadensis leaf juice, water.

Package Label - Principal Display Panel

1000 PCS NDC: 78028-331-01